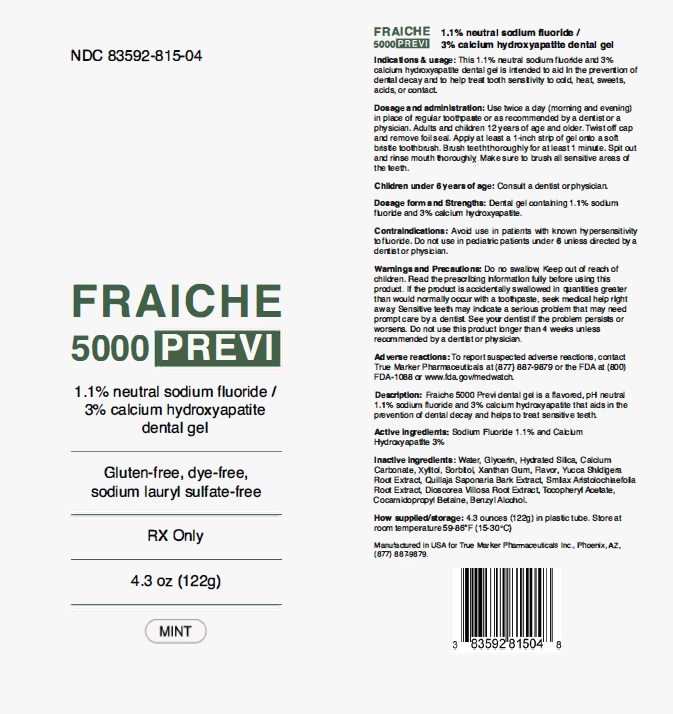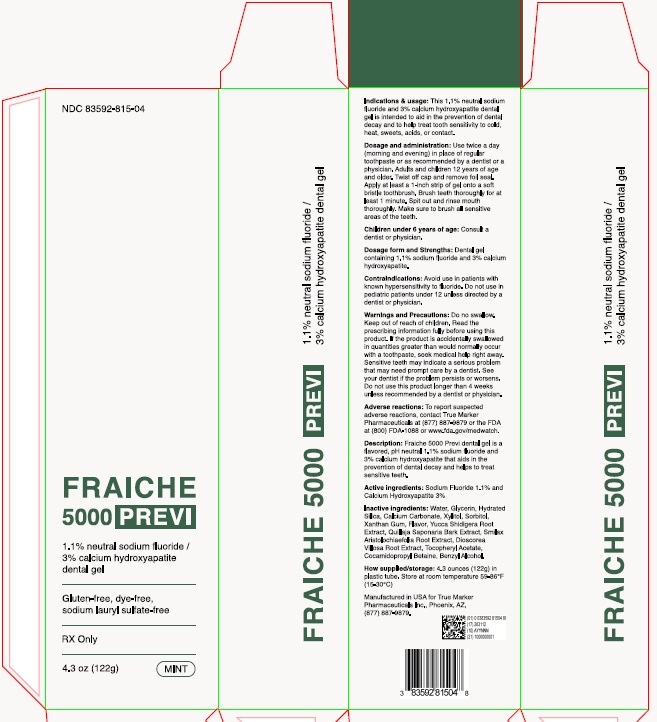 DRUG LABEL: FRAICHE 5000 PREVI
NDC: 83592-815 | Form: GEL
Manufacturer: True Marker Pharmaceuticals, Inc.
Category: prescription | Type: HUMAN PRESCRIPTION DRUG LABEL
Date: 20240314

ACTIVE INGREDIENTS: SODIUM FLUORIDE 1.1 g/100 g; TRIBASIC CALCIUM PHOSPHATE 3 g/100 g
INACTIVE INGREDIENTS: WATER; GLYCERIN; HYDRATED SILICA; CALCIUM CARBONATE; XYLITOL; SORBITOL; XANTHAN GUM; YUCCA SCHIDIGERA WHOLE; QUILLAJA SAPONARIA BARK; SMILAX ARISTOLOCHIIFOLIA ROOT; DIOSCOREA VILLOSA ROOT; .ALPHA.-TOCOPHEROL ACETATE; COCAMIDOPROPYL BETAINE; BENZYL ALCOHOL

Drug Facts

Active Ingredient (s)

Sodium Fluoride 1.1% and Calcium Hydroxyapatite 3%

Uses

This 1.1% neutral sodium fluoride and 3% calcium hydroxyapatite dental gel is intended to aid in the prevention of dental decay and to help treat tooth sensitivity to cold, heat, sweets, acids, or contact.

Warnings

Do no swallow. Keep out of reach of children. Read the prescribing information fully before using this product. If the product is accidentally swallowed in quantities greater than would normally occur with a toothpaste, seek medical help right away. Sensitive teeth may indicate a serious problem that may need prompt care by a dentist. See your dentist if the problem persists or worsens. Do not use this product longer than 4 weeks unless recommended by a dentist or physician.

Adverse reactions

To report suspected adverse reactions, contact True Marker Pharmaceuticals at (877) 887-9879 or the FDA at (800) FDA-1088 or www.fda.gov/medwatch.

Children under 6 years of age

Consult a dentist or physician.

Directions

Use twice a day (morning and evening) in place of regular toothpaste or as recommended by a dentist or a physician. Adults and children 6 years of age and older. Twist off cap and remove foil seal. Apply at least a 1-inch strip of gel onto a soft bristle toothbrush. Brush teeth thoroughly for at least 1 minute. Spit out and rinse mouth thoroughly. Make sure to brush all sensitive areas of the teeth.
Children under 6 years of age: Consult a dentist or physician.

Dosage form and Strengths

Dental gel containing 1.1 % sodium fluoride and 3% calcium hydroxyapatite.

Contraindications

Avoid use in patients with known hypersensitivity to fluoride. Do not use in pediatric patients under 6 unless directed by a dentist or physician.

Description

Fraiche 5000 Previ dental gel is a flavored, pH neutral 1.1 % sodium fluoride and 3% calcium hydroxyapatite that aids in the prevention of dental decay and helps to treat sensitive teeth.

Inactive Ingredients

Water, Glycerin, Hydrated Silica, Calcium Carbonate, Xylitol, Sorbitol, Xanthan Gum, Flavor, Yucca Shidigera Root Extract, Quillaja Saponaria Bark Extract, Smilax Aristolochiaefolia Root Extract, Dioscorea Villosa Root Extract, Tocopheryl Acetate, Cocamidopropyl Betaine, Benzyl Alcohol.

How supplied/storage

4.3 ounces (122g) in plastic tube. Store at room temperature 59-86° F
(15-30 - °C)